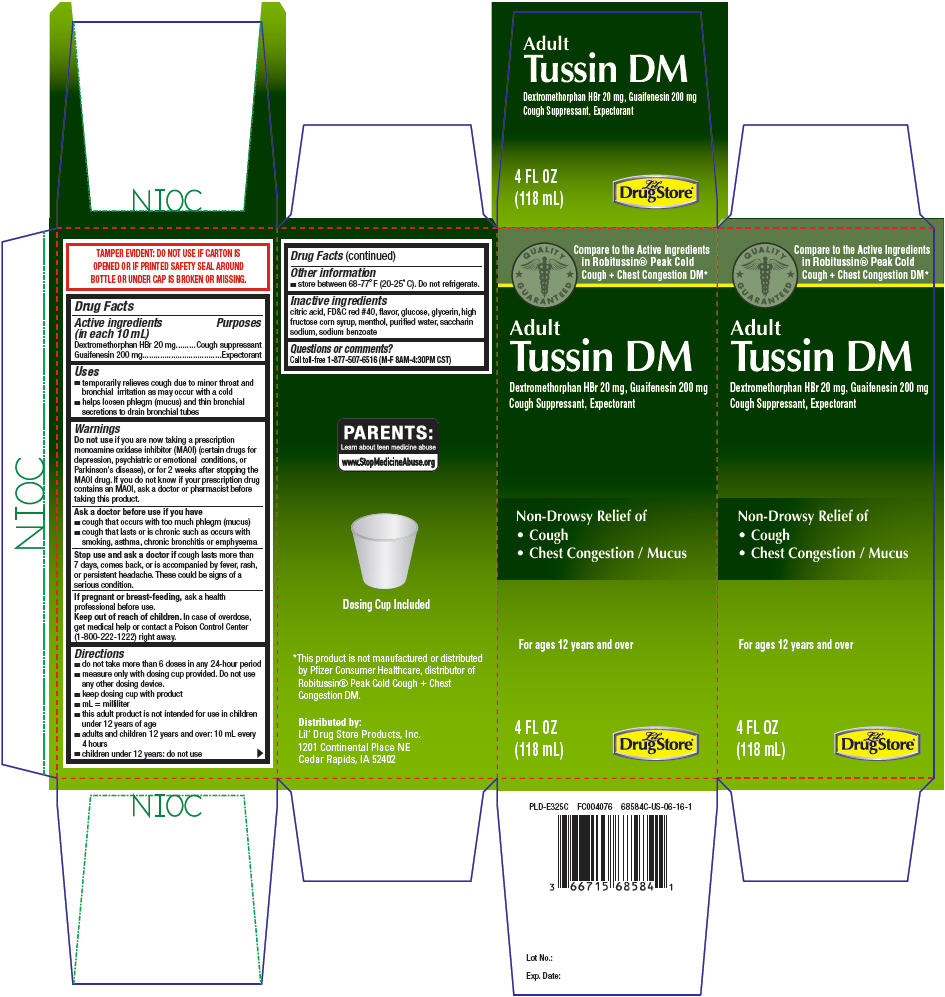 DRUG LABEL: Adult Tussin DM
NDC: 66715-6858 | Form: LIQUID
Manufacturer: Lil' Drug Store Products, Inc
Category: otc | Type: HUMAN OTC DRUG LABEL
Date: 20241231

ACTIVE INGREDIENTS: DEXTROMETHORPHAN HYDROBROMIDE 10 mg/5 mL; GUAIFENESIN 100 mg/5 mL
INACTIVE INGREDIENTS: CITRIC ACID MONOHYDRATE; FD&C RED NO. 40; DEXTROSE, UNSPECIFIED FORM; GLYCERIN; HIGH FRUCTOSE CORN SYRUP; MENTHOL, UNSPECIFIED FORM; WATER; SACCHARIN SODIUM; SODIUM BENZOATE

Lil' Drug Store® Adult Tussin DM

Drug Facts

ACTIVE INGREDIENT

PURPOSE

Active ingredients (in each 10 mL) | Purposes
Dextromethorphan HBr 20 mg | Cough suppressant
Guaifenesin 200 mg | Expectorant

Uses

- temporarily relieves cough due to minor throat and bronchial irritation as may occur with a cold
- helps loosen phlegm (mucus) and thin bronchial secretions to drain bronchial tubes

Warnings

Do not use if you are now taking a prescription monoamine oxidase inhibitor (MAOI) (certain drugs for depression, psychiatric or emotional conditions, or Parkinson's disease), or for 2 weeks after stopping the MAOI drug. If you do not know if your prescription drug contains an MAOI, ask a doctor or pharmacist before taking this product.

Ask a doctor before use if you have

- cough that occurs with too much phlegm (mucus)
- cough that lasts or is chronic such as occurs with smoking, asthma, chronic bronchitis or emphysema

Stop use and ask a doctor if cough lasts more than 7 days, comes back, or is accompanied by fever, rash, or persistent headache. These could be signs of a serious condition.

PREGNANCY OR BREAST FEEDING

If pregnant or breast-feeding, ask a health professional before use.

Keep out of reach of children. In case of overdose, get medical help or contact a Poison Control Center (1-800-222-1222) right away.

Directions

- do not take more than 6 doses in any 24-hour period
- measure only with dosing cup provided. Do not use any other dosing device.
- keep dosing cup with product
- mL = milliliter
- this adult product is not intended for use in children under 12 years of age
- adults and children 12 years and over: 10 mL every 4 hours
- children under 12 years: do not use

Other information

- store between 68-77° F (20-25° C). Do not refrigerate.

Inactive ingredients

citric acid, FD&C red #40, flavor, glucose, glycerin, high fructose corn syrup, menthol, purified water, saccharin sodium, sodium benzoate

Questions or comments?

Call toll-free 1-877-507-6516 (M-F 8AM-4:30PM CST)

Distributed by:
Lil' Drug Store Products, Inc.
1201 Continental Place NE
Cedar Rapids, IA 52402

PRINCIPAL DISPLAY PANEL - 118 mL Bottle Carton

QUALITY
GUARANTEED

Compare to the Active Ingredients
in Robitussin® Peak Cold
Cough + Chest Congestion DM*

Adult
Tussin DM

Dextromethorphan HBr 20 mg, Guaifenesin 200 mg
Cough Suppressant, Expectorant

Non-Drowsy Relief of

- Cough
- Chest Congestion / Mucus

For ages 12 years and over

4 FL OZ
(118 mL)

Lil'
Drug Store®